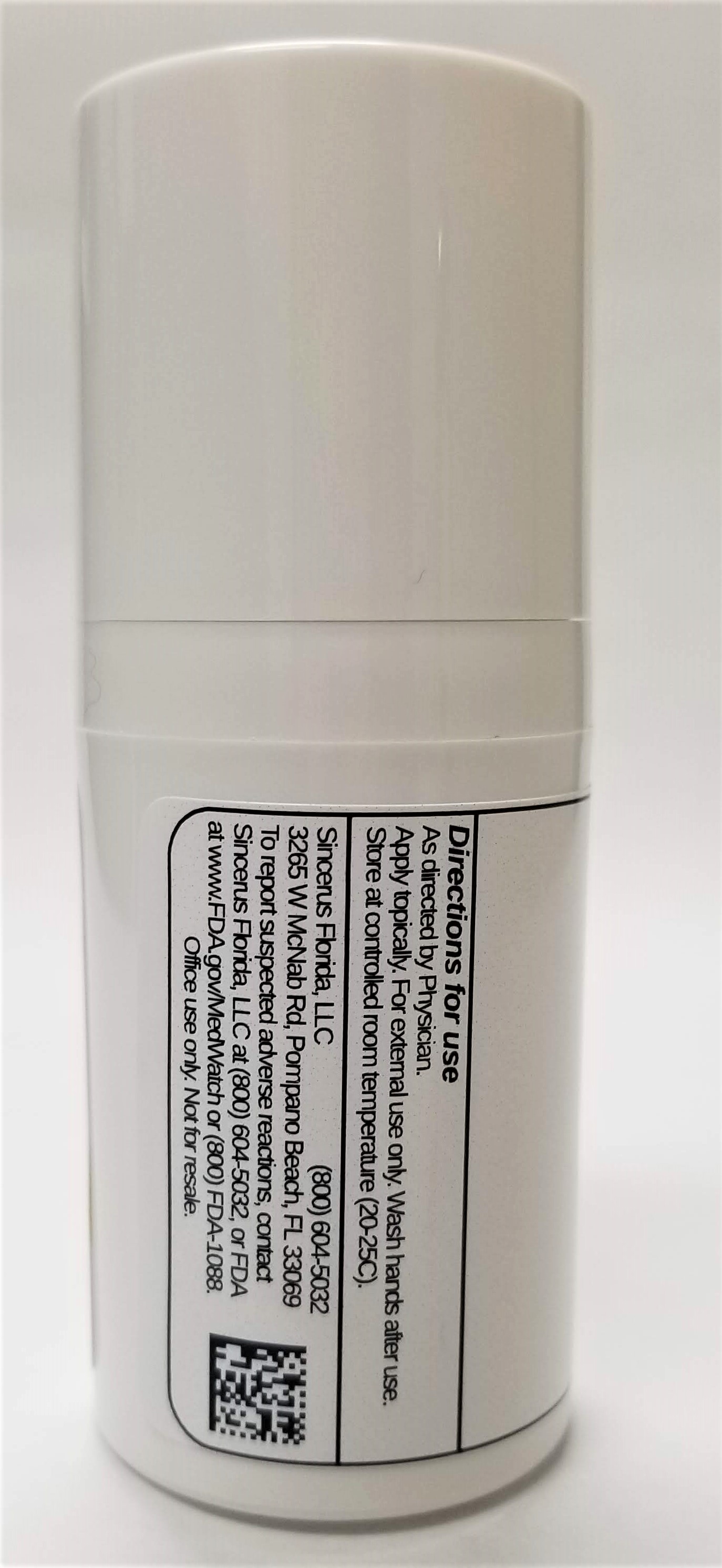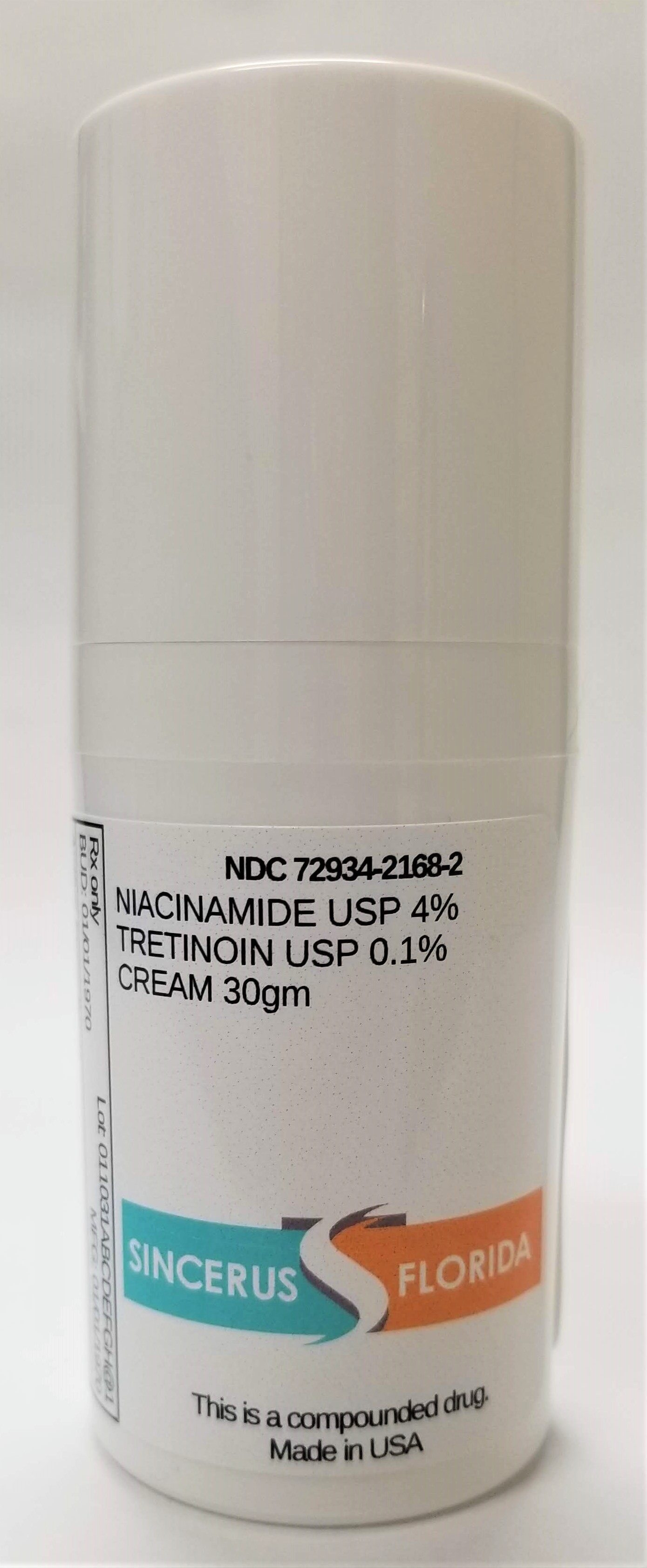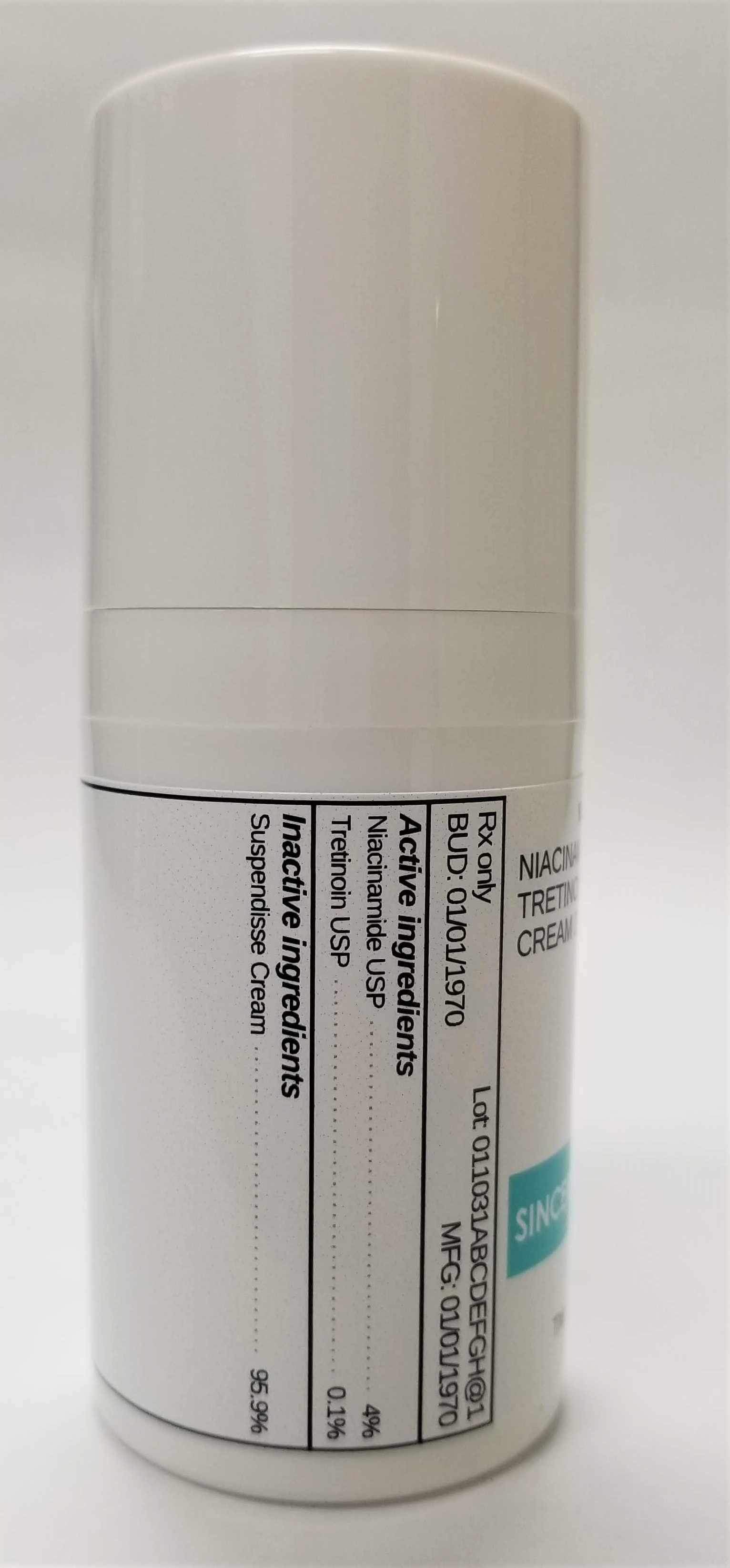 DRUG LABEL: NIACINAMIDE 4% / TRETINOIN 0.1%
NDC: 72934-2168 | Form: CREAM
Manufacturer: Sincerus Florida, LLC
Category: prescription | Type: HUMAN PRESCRIPTION DRUG LABEL
Date: 20200128

ACTIVE INGREDIENTS: NIACINAMIDE 4 g/100 g; TRETINOIN 0.1 g/100 g

NIACINAMIDE 4%/ TRETINOIN 0.1%